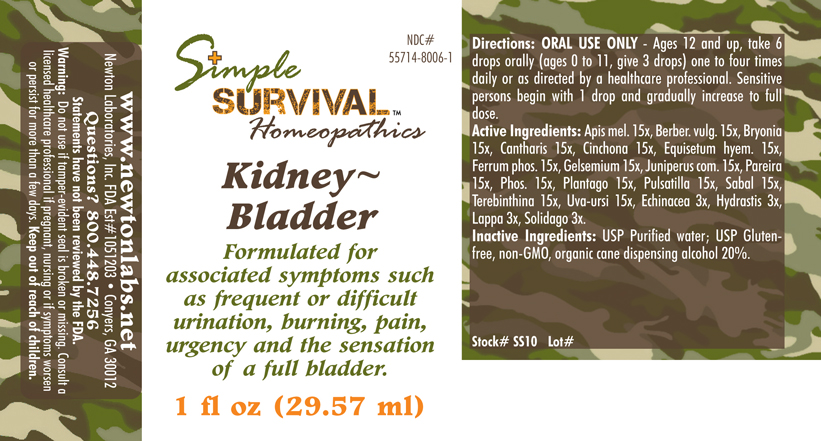 DRUG LABEL: Kidney - Bladder 
NDC: 55714-8006 | Form: LIQUID
Manufacturer: Newton Laboratories, Inc.
Category: homeopathic | Type: HUMAN OTC DRUG LABEL
Date: 20140415

ACTIVE INGREDIENTS: Apis Mellifera 15 [hp_X]/1 mL; Berberis Vulgaris Root Bark 15 [hp_X]/1 mL; Bryonia Alba Root 15 [hp_X]/1 mL; Lytta Vesicatoria 15 [hp_X]/1 mL; Cinchona Officinalis Bark 15 [hp_X]/1 mL; Equisetum Hyemale 15 [hp_X]/1 mL; Ferrosoferric Phosphate 15 [hp_X]/1 mL; Gelsemium Sempervirens Root 15 [hp_X]/1 mL; Juniper Berry 15 [hp_X]/1 mL; Chondrodendron Tomentosum Root 15 [hp_X]/1 mL; Phosphorus 15 [hp_X]/1 mL; Plantago Major 15 [hp_X]/1 mL; Pulsatilla Vulgaris 15 [hp_X]/1 mL; Saw Palmetto 15 [hp_X]/1 mL; Turpentine Oil 15 [hp_X]/1 mL; Arctostaphylos Uva-ursi Leaf 15 [hp_X]/1 mL; Echinacea, Unspecified 3 [hp_X]/1 mL; Goldenseal 3 [hp_X]/1 mL; Arctium Lappa Root 3 [hp_X]/1 mL; Solidago Virgaurea Flowering Top 3 [hp_X]/1 mL
INACTIVE INGREDIENTS: Alcohol

Kidney - Bladder

INDICATIONS & USAGE SECTION

Kidney - Bladder Formulated for associated symptoms such as frequent or difficult urination, burning, pain, urgency and the sensation of a full bladder.

DOSAGE & ADMINISTRATION SECTION

Directions: ORAL USE ONLY - Ages 12 and up, take 6 drops orally (ages 0 to 11, give 3 drops) one to four times daily or as directed by a healthcare professional. Sensitive persons begin with 1 drop and gradually increase to full dose.

OTC - ACTIVE INGREDIENT SECTION

Apis mel. 15x, Berber. vulg. 15x, Bryonia 15x, Cantharis 15x, Cinchona 15x, Equisetum hyem. 15x, Ferrum phos. 15x, Gelsemium 15x, Juniperus com. 15x, Pareira 15x, Phos. 15x, Plantago 15x, Pulsatilla 15x, Sabal 15x, Terebinthina 15x, Uva-ursi 15x, Echinacea 3x, Hydrastis 3x, Lappa 3x, Solidago 3x.

OTC - PURPOSE SECTION

Formulated for associated symptoms such as frequent or difficult urination, burning, pain, urgency and the sensation of a full bladder.

INACTIVE INGREDIENT SECTION

Inactive Ingredients: USP Purified Water; USP Gluten-free, non-GMO, organic cane dispensing alcohol 20%.

QUESTIONS SECTION

www.newtonlabs.net Newton Laboratories, Inc. FDA Est # 1051203 - Conyers, GA 30012
Questions? 1.800.448.7256

WARNINGS SECTION

Warning: Do not use if tamper - evident seal is broken or missing. Consult a licensed healthcare professional if pregnant, nursing or if symptoms worsen or persist for more than a few days. Keep out of reach of children

OTC - PREGNANCY OR BREAST FEEDING SECTION

Consult a licensed healthcare professional if pregnant, nursing or if symptoms worsen or persist for more than a few days.

OTC - KEEP OUT OF REACH OF CHILDREN SECTION

Keep out of reach of children